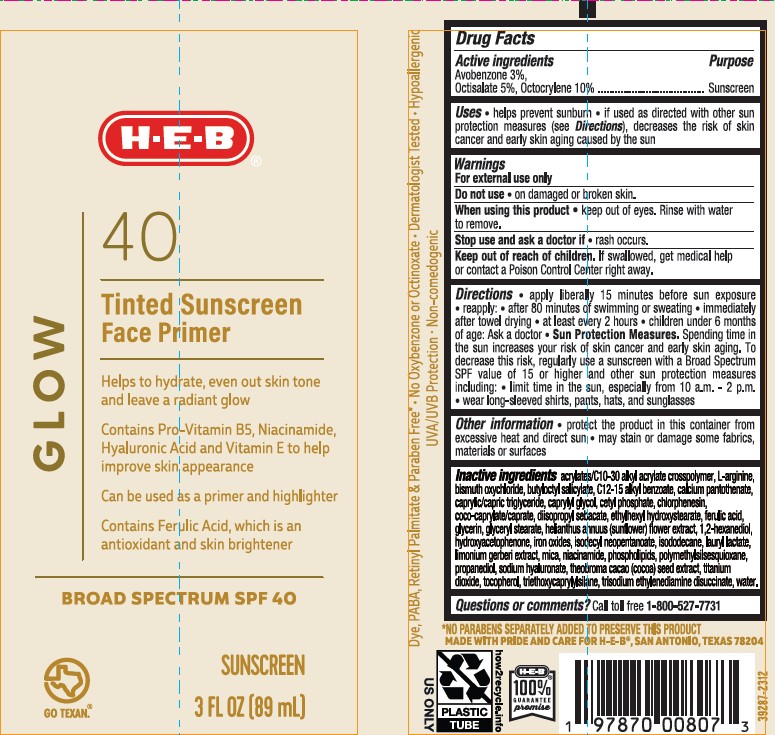 DRUG LABEL: HEB Glow 40 Tinted Sunscreen Face Primer
NDC: 37808-154 | Form: CREAM
Manufacturer: H.E.B.
Category: otc | Type: HUMAN OTC DRUG LABEL
Date: 20250326

ACTIVE INGREDIENTS: AVOBENZONE 30 mg/1 mL; OCTISALATE 50 mg/1 mL; OCTOCRYLENE 100 mg/1 mL
INACTIVE INGREDIENTS: COCO-CAPRYLATE/CAPRATE; ETHYLHEXYL HYDROXYSTEARATE; WATER; .ALPHA.-TOCOPHEROL, DL-; MICA; CAPRYLYL GLYCOL; TITANIUM DIOXIDE; FERRIC OXIDE YELLOW; COCOA; OMEGA-3 FATTY ACIDS; CARBOMER COPOLYMER TYPE A (ALLYL PENTAERYTHRITOL CROSSLINKED); FERULIC ACID; LIMONIUM GERBERI FLOWERING TOP; TRISODIUM ETHYLENEDIAMINE DISUCCINATE; BISMUTH OXYCHLORIDE; STANNIC OXIDE; BUTYLOCTYL SALICYLATE; ALKYL (C12-15) BENZOATE; CETYL PHOSPHATE; CHLORPHENESIN; DIISOPROPYL SEBACATE; ISODODECANE; ARGININE; NIACINAMIDE; PROPANEDIOL; ISODECYL NEOPENTANOATE; LAURYL LACTATE; GLYCERIN; GLYCERYL 1-STEARATE; HELIANTHUS ANNUUS FLOWERING TOP; HYDROXYACETOPHENONE; TRIETHOXYCAPRYLYLSILANE; PANTOTHENIC ACID; POLYMETHYLSILSESQUIOXANE (11 MICRONS); HYALURONATE SODIUM; 1,2-HEXANEDIOL

HEB Glow 40 Tinted Sunscreen Face Primer

Active Ingredients

Acobenzone 3.0%, Octisalate 5.0%, Octocrylene 10.0%

Purpose

Sunscreen

Uses

- Helps prevent sunburn
- If used as directed with other sun protection measures (see Directions), decreases the risk of skin cancer and early skin aging caused by the sun

Warnings

For external use only

Do not use

• on damaged or broken skin

When using this product

keep out of eyes. Rinse with water to remove.

Stop use and ask doctor if

• rash occurs

Keep out of reach of children.

If swallowed, get medical help or contact a Poison Control Center right away.

Directions

- apply liberally 15 minutes before sun exposure
- reapply:

• after 80 minutes of swimming or sweating

• immediately after towel drying

• at least every 2 hours

- children under 6 months of age: Ask a doctor
- Sun Protection Measures. Spending time in the sun increases your risk of skin cancer and early aging. To decrease this risk, regularly use a sunscreen with a Broad Spectrum value of 15 or higher and other sun protection measures including:

• limit time in the sun, especially from 10am-2pm

• wear long-sleeved shirts, pants, hats, and sunglasses.

Other Information

- protect the product in this container from excessive heat and direct sun
- may stain or damage some fabrics, materials or surfaces

Inactive Ingredient(s)

acrylates/C10-30 alkyl acrylate crosspolymer, L-arginine, bismuth oxychloride, butyloctyl salicylate, C12-15 alkyl benzoate, calcium pantothenate, caprylic/capric triglyceride, caprylyl glycol, cetyl phosphate, chlorphenesin, coco-caprylate/caprate, diisopropyl sebacate, ethylhexyl hydroxystearate, ferulic acid, glycerin, glyceryl stearate, helianthus annuus (sunflower) flower extract, 1,2-hexanediol, hydroxyacetophenone, iron oxides, isodecyl neopentanoate, isododecane, lauryl lactate, limonium gerberi extract, mica, niacinamide, phospholipids, polymethylsilsesquioxane, propanediol, sodium hyaluronate, theobroma cacao (cocoa) seed extract, titanium dioxide, tocopherol, triethoxycaprylylsilane, trisodium ethylenediamine disuccinate, water